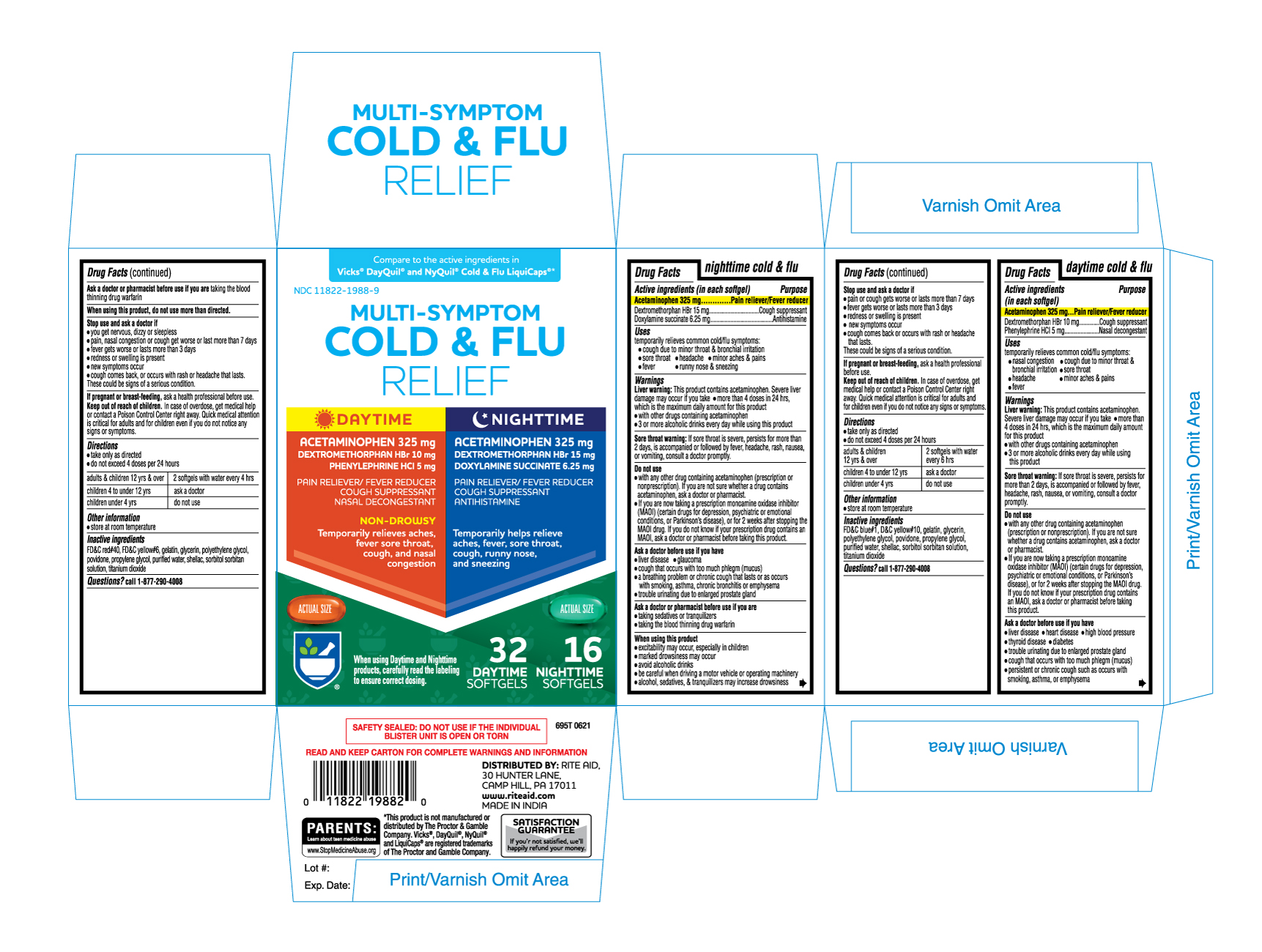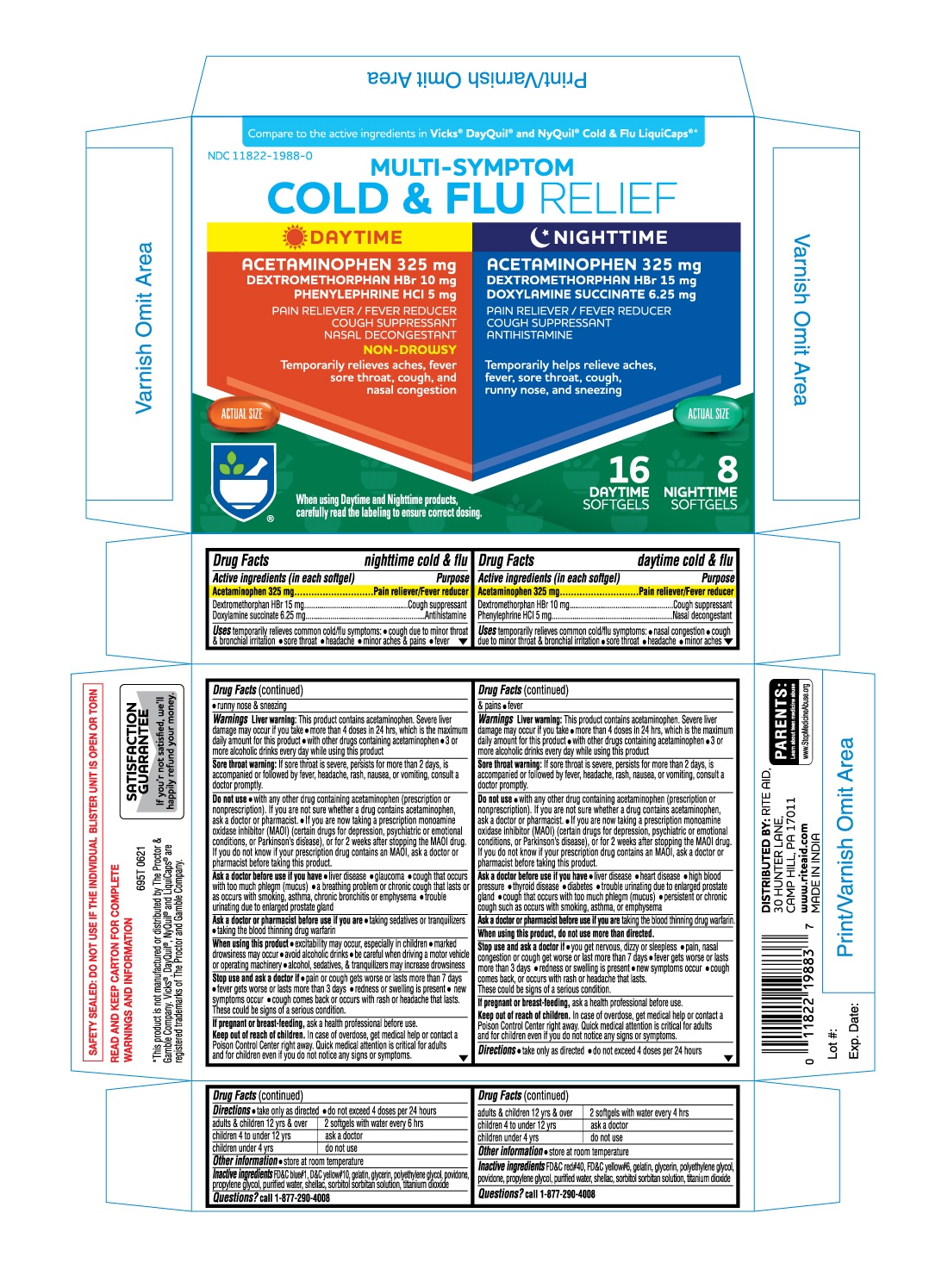 DRUG LABEL: MULTI-SYMPTOM COLD AND FLU RELIEF DAYTIME NIGHTTIME
NDC: 11822-1988 | Form: KIT | Route: ORAL
Manufacturer: RITE AID
Category: otc | Type: HUMAN OTC DRUG LABEL
Date: 20221226

ACTIVE INGREDIENTS: DEXTROMETHORPHAN HYDROBROMIDE 10 mg/1 1; PHENYLEPHRINE HYDROCHLORIDE 5 mg/1 1; ACETAMINOPHEN 325 mg/1 1; DOXYLAMINE SUCCINATE 6.25 mg/1 1; ACETAMINOPHEN 325 mg/1 1; DEXTROMETHORPHAN HYDROBROMIDE 15 mg/1 1
INACTIVE INGREDIENTS: FD&C RED NO. 40; FD&C YELLOW NO. 6; SORBITAN; SHELLAC; PROPYLENE GLYCOL; POLYETHYLENE GLYCOL, UNSPECIFIED; POVIDONE; WATER; TITANIUM DIOXIDE; GELATIN; GLYCERIN; SORBITAN; FD&C BLUE NO. 1; GLYCERIN; WATER; SHELLAC; PROPYLENE GLYCOL; TITANIUM DIOXIDE; D&C YELLOW NO. 10; GELATIN; POLYETHYLENE GLYCOL, UNSPECIFIED; POVIDONE

695T RITE AID 11822-1988 Multi-Symptom Cold & Flu Relief Daytime Nighttime (Acetaminophen 325mg Dextromethorphan HBr10mg Phenylephrine HCl 5mg Acetaminophen 325mg Dextromethorphan HBr 15mg Doxylamine Succinate 6.25mg)

ACTIVE INGREDIENT

daytime cold &flu
Active ingredients (in each softgel)
Acetaminophen 325 mg
Dextromethorphan HBr 10 mg
Phenylephrine HCl 5 mg

nighttime cold &flu
Active ingredients (in each softgel)
Acetaminophen 325 mg
Dextromethorphan HBr 15 mg
Doxylamine succinate 6.25 mg

PURPOSE

daytime cold & flu
Purpose
Pain reliever/Fever reducer
Cough suppressant
Nasal decongestant

nighttime cold & flu
Purpose
Pain reliever/Fever reducer
Cough suppressant
Antihistamine

Uses
temporarily relieves common cold/flu symptoms:

- nasal congestion (Daytime only)
- cough due to minor throat & bronchial irritation
- sore throat
- headache
- minor aches & pains
- fever
- runny nose & sneezing (Nithttime only)

Warnings

liver warning: This product contains acetaminophen. Severe liver damage may occur if you take

- more than 4 doses in 24 hrs, which is the maximum daily amount for this product
- wtth other drugs containing acetaminophen
- 3 or more alcoholic drinks every day while using this product

Sore throat warning: If sore throat is severe, persists for more than 2 days, is accompanied or followed by fever, headache, rash, nausea, or vomiting, consult a doctor promptly.

Do not use

- with any other drug containing acetaminophen (prescription or nonprescription). If you are not sure whether a drug contains acetaminophen, ask a doctor or pharmacist.
- If you are now taking a prescription monoamine oxidase inhibitor (MAOI) (certain drugs for depression, psychiatric or emotional

conditions, or Parkinson's disease), or for 2 weeks after stopping the MAOI drug. If you do not know if your prescription drug contains an MAOI, ask a doctor or pharmacist before taking this product.

Ask a doctor before use if you have

- liver disease
- glaucoma (nighttime only)
- heart disease (Daytime only)
- high blood pressure (Daytime only)
- thyroid disease (Daytime only)
- diabetes (Daytime only)
- trouble urinating due to enlarged prostate gland
- cough that occurs with too much phlegm (mucus)
- persistent or chronic cough such as occurs with smoking, asthma, or emphysema (Daytime only)
- a breathing problem or chronic cough that lasts or as occurs wtth smoking, asthma, chronic bronchitis or emphysema (nighttime only)

Ask a doctor or pharmacist before use if you are taking sedatives or tranquilizers

- taking the blood thining drug warfarin

When using this product, do not use more than directed.(daytime only)

- excitability may occur, especially in children (nighttime only)
- marked drowsiness may occur (nighttime only)
- avoid alcoholic drinks (nighttime only)
- be carefull when driving a motor vehicle or operating machinery. (nighttime only)
- alcohol, sedatives, & tranquilizers may increase drowsiness. (nighttime only)

Stop use and ask a doctor if

- you get nervous, dizzy or sleepless (daytime only)
- pain, nasal congestion or cough get worse or last more than 7 days (daytime only)
- pain or cough gets worse or lasts more than 7 days (nighttime only)
- fever gets worse or lasts more than 3 days
- redness or swelling is present
- new symptoms occur
- cough comes back, or occurs with rash or headache that lasts.

These could be Signs of a serious condition.

PREGNANCY OR BREAST FEEDING

If pregnant or breast-feeding, ask a health professional before use.

Keep out of reach of children. In case of overdose, get medical help or contact a Poison Control Center right away. Quick medical attention is critical for adults and for children even if you do not notice any signs or symptoms.

Directions

- take only as directed
- do not exceed 4 doses per 24 hours

adults & children 12 yrs & over: 2 softgels with water every 4 hrs (daytime only)
adults & children 12 yrs & over: 2 softgels with water every 6 hrs (nighttime only)
children 4 to under 12 yrs:ask a doctor
children under 4 yrs:do not use

OTHER INFORMATION

- store at room temperature

INACTIVE INGREDIENT

daytime cold & flu

Inactive ingredients FD&C red#40, FD&C yellow#6, gelatin, glycerin, polyethylene glycol,
povidone, propylene glycol, purified water, shellac, sorbitol sorbitan solution, titanium dioxide

nighttime cold & flu

Inactive ingredients FD&C blue#1, D&C yellow#10, gelatin, glycerin, polyethylene glycol,
povidone, propylene glycol, purified water, shellac, sorbitol sorbitan solution, titanium dioxide

Questions?call 1-877-290-4008